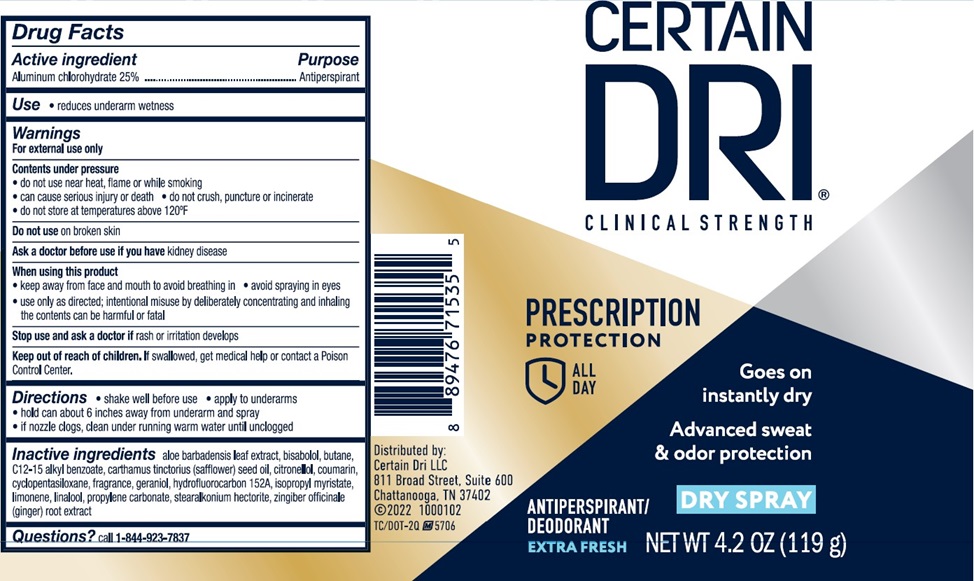 DRUG LABEL: CERTAIN DRI
NDC: 69693-720 | Form: SPRAY
Manufacturer: Clarion Brands, LLC
Category: otc | Type: HUMAN OTC DRUG LABEL
Date: 20251226

ACTIVE INGREDIENTS: ALUMINUM CHLOROHYDRATE 25 g/100 mL
INACTIVE INGREDIENTS: ALOE VERA LEAF; LEVOMENOL; BUTANE; ALKYL (C12-15) BENZOATE; SAFFLOWER OIL; COUMARIN; CYCLOMETHICONE 5; GERANIOL; 1,1-DIFLUOROETHANE; ISOPROPYL MYRISTATE; LIMONENE, (+)-; LINALOOL, (+/-)-; PROPYLENE CARBONATE; STEARALKONIUM HECTORITE; GINGER; .BETA.-CITRONELLOL, (R)-

Drug Facts

Active Ingredient | Purpose
Aluminum Chlorohydrate 25% | Antiperspirant

Uses

- reduces underarm wetness

Warnings For external use only

- EXTREMELY FLAMMABLE. DO NOT USE NEAR HEAT, FLAME OR WHILE SMOKING. CAN CAUSE SERIOUS INJURY OR DEATH.
- Keep away from face and mouth to avoid breathing in.
- Avoid spraying in eyes. Contents under pressure. Do not puncture or incinerate. Do not expose to heat or store at temperature above 120°F/50° or in enclosed places that could overheat.
- Do not use on broken skin. Stop use if rash or irritation occurs.
- Ask a doctor before using if you have kidney disease.

USE ONLY AS DIRECTED, INTENTIONAL MISUSE BY DELIBERATELY CONCENTRATING AND INHALING THE CONTENTS CAN BE HARMFUL OR FATAL.

PREGNANCY OR BREAST FEEDING

If pregnant or breast-feeding,ask a health professional before use.

KEEP OUT OF REACH OF CHILDREN. If swallowed, get medical help or contact a Poison Control Center.

Directions

apply to underarms

Inactive ingredients

Aloe Barbadensis Leaf Extract, Bisabolol, Butane, C12-15 Alkyl Benzoate, Carthamus Tinctorius (Safflower) Seed Oil, Cintronellol, Coumarin, Cyclopentasiloxane, Fragrance, Geraniol, Hydrofluorocarbon 152A, Isopropyl Myristate, Limonene, Linalool, Propylene Carbonate, Stearalkonium Hectorite, Zingiber Officinale (Ginger) Root Extract

Questions? Call 1-844-923-7837

PRINCIPAL DISPLAY PANEL

CERTAIN
DRI®
Clinical Strength

PRESCRIPTION
PROTECTION
ALL DAY
Goes on Instantly Dry
Advanced Sweat and Odor Protection
DRY SPRAY
ANTIPERSPIRANT/
DEODORANT
EXTRA FRESH
NET WT 4.2 oz (119 g)
Distributed by:
Certain Dri LLC
811 Broad Street. Suite 600
Chattanooga, TN 37402
©2022 1000102
TC/DOT-2Q M5706